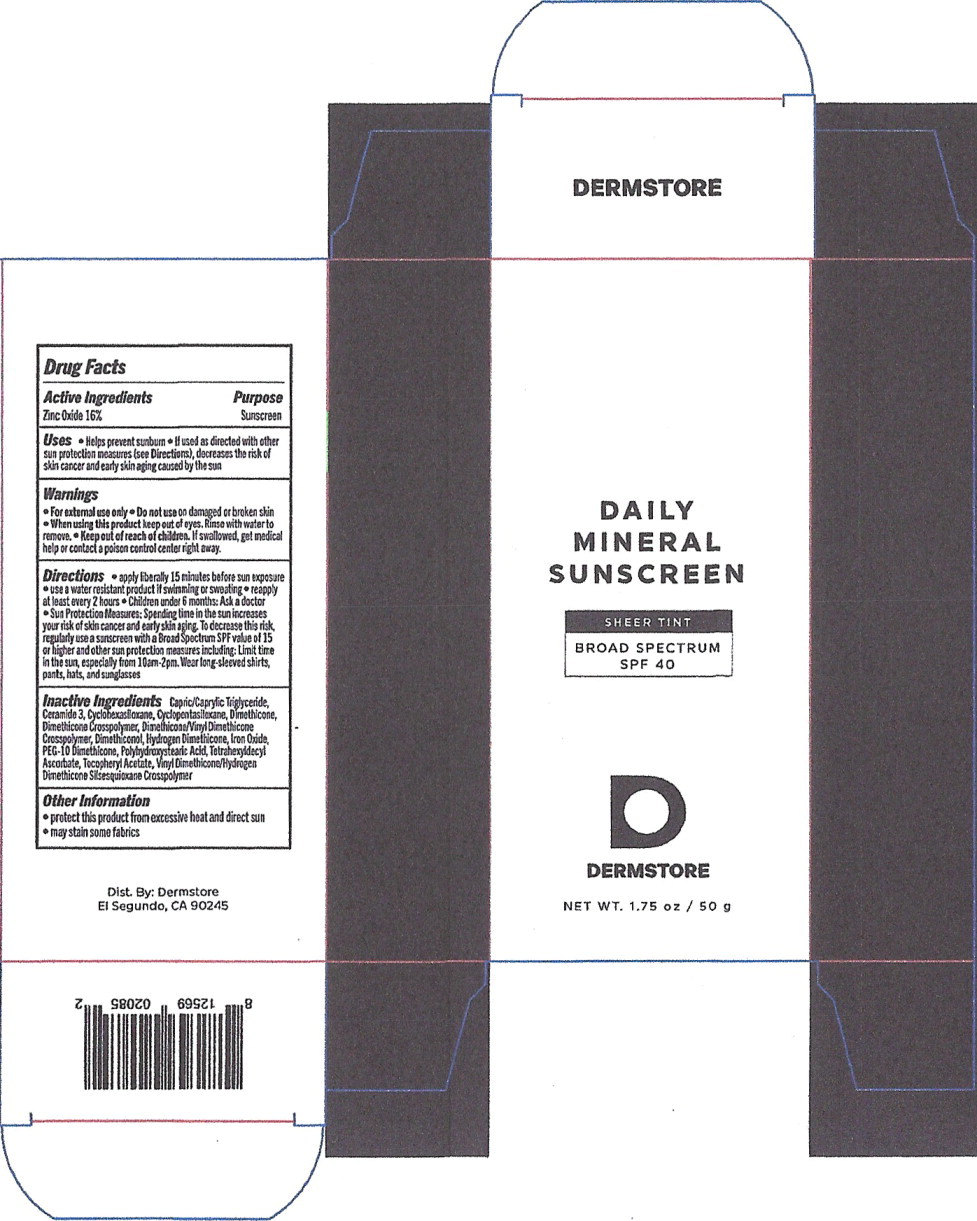 DRUG LABEL: Daily Mineral Sunscreen
NDC: 12569-020 | Form: CREAM
Manufacturer: Dermstore.com
Category: otc | Type: HUMAN OTC DRUG LABEL
Date: 20200929

ACTIVE INGREDIENTS: Zinc Oxide 160 mg/1 g
INACTIVE INGREDIENTS: MEDIUM-CHAIN TRIGLYCERIDES; CERAMIDE NP; Cyclomethicone 6; Cyclomethicone 5; Dimethicone 20; Dimethicone Crosspolymer (450000 MPA.S AT 12% in Cyclopentasiloxane); Dimethicone/Vinyl Dimethicone Crosspolymer (Soft Particle); Dimethiconol (2000 CST); Brown Iron Oxide; Hydrogen Dimethicone (20 CST); PEG-10 Dimethicone (600 CST); POLYHYDROXYSTEARIC ACID (2300 MW); TETRAHEXYLDECYL ASCORBATE; .ALPHA.-TOCOPHEROL ACETATE; VINYL DIMETHICONE/METHICONE SILSESQUIOXANE CROSSPOLYMER

Drug Facts

Active Ingredients

Zinc Oxide 16%

Purpose

Sunscreen

Uses

- Helps prevent sunburn
- If used as directed with other sun protection measures (see Directions), decreases the risk of skin cancer and early skin aging caused by the sun

Warnings

- For external use only

- Do not use on damaged or broken skin

- When using this product keep out of eyes. Rinse with water to remove.

- Keep out of reach of children, if swallowed, get medical help or contact a poison control center right away.

Directions

- apply liberally 15 minutes before sun exposure
- use a water resistant product if swimming or sweating
- reapply at least every 2 hours
- Children under 6 months: Ask a doctor
- Sun Protection measures: Spending time in the sun increases your risk of skin cancer and early skin aging. To decrease this risk, regularly use a sunscreen with a Broad Spectrum SPF value of 15 or higher and other sun protection measures including: Limit time in the sun, especially from 10am-2pm. Wear long-sleeved shirts, pants, hats, and sunglasses

Inactive Ingredients

Capric/Caprylic Triglyceride, Ceramide 3, Cyclohexasiloxane, Cyclopentasiloxane, Dimethicone, Dimethicone Crosspolymer, Dimethicone/Vinyl Dimethicone Crosspolymer, Dimethiconol, Hydrogen Dimethicone, Iron Oxide, PEG-10 Dimethicone, Polyhydroxystearic Acid, Tetrahexyldecyl Ascorbate, Tocopheryl Acetate, Vinyl Dimethicone/Hydrogen Dimethicone Silsesquioxane Crosspolymer

Other Information

- protect this product from excessive heat and direct sun
- may stain some fabrics

Principal Display Panel – 1.75 oz Carton Label

DAILY
MINERAL
SUNSCREEN

SHEER TINT

BROAD SPECTRUM
SPF 40

DERMSTORE

NET WT. 1.75 oz / 50 g